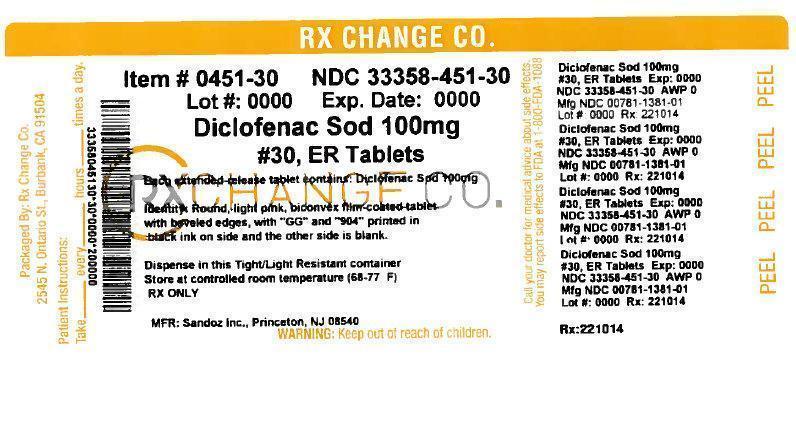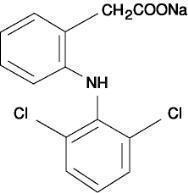 DRUG LABEL: Diclofenac Sodium
NDC: 33358-451 | Form: TABLET, FILM COATED, EXTENDED RELEASE
Manufacturer: RxChange Co.
Category: prescription | Type: HUMAN PRESCRIPTION DRUG LABEL
Date: 20141202

ACTIVE INGREDIENTS: DICLOFENAC SODIUM 100 mg/1 1
INACTIVE INGREDIENTS: CETYL ALCOHOL; HYDROXYPROPYL CELLULOSE (TYPE H); FERRIC OXIDE RED; MAGNESIUM STEARATE; POLYETHYLENE GLYCOLS; POVIDONES; SILICON DIOXIDE; SUCROSE; TALC; TITANIUM DIOXIDE

Diclofenac Sodium
Extended-Release Tablets, USP
Tablets of 100 mg
Rx only
Prescribing Information

BOXED WARNING

Cardiovascular Risk

- NSAIDs may cause an increased risk of serious cardiovascular thrombotic events, myocardial infarction, and stroke, which can be fatal. This risk may increase with duration of use. Patients with cardiovascular disease or risk factors for cardiovascular disease may be at greater risk. (See WARNINGS.)
- Diclofenac sodium extended-release tablets, USP are contraindicated for the treatment of perioperative pain in the setting of coronary artery bypass graft (CABG) surgery (see WARNINGS).

Gastrointestinal Risk

- NSAIDs cause an increased risk of serious gastrointestinal adverse events including inflammation, bleeding, ulceration, and perforation of the stomach or intestines, which can be fatal. These events can occur at any time during use and without warning symptoms. Elderly patients are at greater risk for serious gastrointestinal events. (See WARNINGS.)

DESCRIPTION

Diclofenac Sodium Extended-Release Tablets, USP is a benzeneacetic acid derivative. Diclofenac sodium extended-release is available as extended-release tablets of 100 mg (light pink) for oral administration. The chemical name is 2-[(2,6-dichlorophenyl)amino] benzeneacetic acid, monosodium salt. The molecular weight is 318.14. Its molecular formula is C14H10Cl2NNaO2, and it has the following structural formula

The inactive ingredients in Diclofenac Sodium Extended-Release Tablets, USP include: cetyl alcohol, hydroxypropyl methylcellulose, iron oxide, magnesium stearate, polyethylene glycol, polysorbate, povidone, silicon dioxide, sucrose, talc, titanium dioxide.

CLINICAL PHARMACOLOGY

Pharmacodynamics

Diclofenac sodium extended-release tablets, USP is a non-steroidal anti-inflammatory drug (NSAID) that exhibits anti-inflammatory, analgesic, and antipyretic activities in animal models. The mechanism of action of diclofenac sodium extended-release tablets, USP, like that of other NSAIDs, is not completely understood but may be related to prostaglandin synthetase inhibition.

Absorption

Diclofenac is 100% absorbed after oral administration compared to IV administration as measured by urine recovery. However, due to first-pass metabolism, only about 50% of the absorbed dose is systemically available (see Table 1). When diclofenac sodium extended-release tablets, USP are taken with food, there is a delay of 1 to 2 hours in the Tmax and a two-fold increase in Cmax values. The extent of absorption of diclofenac, however, is not significantly affected by food intake.

Table 1. Pharmacokinetic Parameters for Diclofenac
PK Parameter | Normal Healthy Adults (18-48 yrs.)
 | Mean | Coefficient of Variation (%)
Absolute Bioavailability (%) [N = 7] | 55 | 40
Tmax (hr) [N = 12] | 5.3 | 28
Oral Clearance (CL/F; mL/min) [N = 12] | 895 | 56
Renal Clearance (% unchanged drug in urine) [N = 7] | <1 | —
Apparent Volume of Distribution (V/F; L/kg) [N = 56] | 1.4 | 58
Terminal Half-life (hr) [N = 56] | 2.3 | 48

Distribution

The apparent volume of distribution (V/F) of diclofenac sodium is 1.4 L/kg. Diclofenac is more than 99% bound to human serum proteins, primarily to albumin. Serum protein binding is constant over the concentration range (0.15-105 μg/mL) achieved with recommended doses.

Diclofenac diffuses into and out of the synovial fluid. Diffusion into the joint occurs when plasma levels are higher than those in the synovial fluid, after which the process reverses and synovial fluid levels are higher than plasma levels. It is not known whether diffusion into the joint plays a role in the effectiveness of diclofenac.

Metabolism

Five diclofenac metabolites have been identified in human plasma and urine. The metabolites include 4'-hydroxy-, 5-hydroxy-, 3'-hydroxy-, 4',5-dihydroxy- and 3'-hydroxy-4'-methoxy- diclofenac. The major diclofenac metabolite, 4'-hydroxy-diclofenac, has very weak pharmacologic activity. The formation of 4’-hydroxy diclofenac is primarily mediated by CPY2C9. Both diclofenac and its oxidative metabolites undergo glucuronidation or sulfation followed by biliary excretion. Acylglucuronidation mediated by UGT2B7 and oxidation mediated by CPY2C8 may also play a role in diclofenac metabolism. CYP3A4 is responsible for the formation of minor metabolites, 5-hydroxy- and 3’-hydroxy-diclofenac. In patients with renal dysfunction, peak concentrations of metabolites 4'-hydroxy- and 5-hydroxy-diclofenac were approximately 50% and 4% of the parent compound after single oral dosing compared to 27% and 1% in normal healthy subjects.

Excretion

Diclofenac is eliminated through metabolismand subsequent urinary and biliary excretion of the glucuronide and the sulfate conjugates of the metabolites. Little or no free unchanged diclofenac is excreted in the urine. Approximately 65% of the dose is excreted in the urine and approximately 35% in the bile as conjugates of unchanged diclofenac plus metabolites.Because renal elimination is not a significant pathway of elimination for unchanged diclofenac, dosing adjustment in patients with mild to moderate renal dysfunction is not necessary. The terminal half-life of unchanged diclofenac is approximately 2 hours.

Drug Interactions

When co-administered with voriconazole (inhibitor of CYP2C9, 2C19 and 3A4 enzyme), the Cmax and AUC of diclofenac increased by 114% and 78%, respectively (see PRECAUTIONS, Drug Interactions).

Special Populations

Pediatric: The pharmacokinetics of diclofenac sodium extended-release tablets, USP has not been investigated in pediatric patients.

Race: Pharmacokinetic differences due to race have not been identified.

Hepatic Insufficiency: Hepatic metabolism accounts for almost 100% of diclofenac sodium elimination, so patients with hepatic disease may require reduced doses of diclofenac sodium extended-release tablets, USP compared to patients with normal hepatic function.

Renal Insufficiency: Diclofenac pharmacokinetics has been investigated in subjects with renal insufficiency. No differences in the pharmacokinetics of diclofenac have been detected in studies of patients with renal impairment. In patients with renal impairment (inulin clearance 60-90, 30-60, and <30 mL/min; N=6 in each group), AUC values and elimination rate were comparable to those in healthy subjects.

INDICATIONS AND USAGE

Carefully consider the potential benefits and risks of Diclofenac Sodium Extended-Release Tablets, USP and other treatment options before deciding to use Diclofenac Sodium Extended-Release Tablets, USP. Use the lowest effective dose for the shortest duration consistent with individual patient treatment goals (see WARNINGS).

Diclofenac Sodium Extended-Release Tablets, USP are indicated:

- For relief of the signs and symptoms of osteoarthritis
- For relief of the signs and symptoms of rheumatoid arthritis

CONTRAINDICATIONS

Diclofenac sodium extended-release tablets, USP is contraindicated in patients with known hypersensitivity to diclofenac.

Diclofenac sodium extended-release tablets, USP should not be given to patients who have experienced asthma, urticaria, or allergic-type reactions after taking aspirin or other NSAIDs. Severe, rarely fatal, anaphylactic-like reactions to NSAIDs have been reported in such patients (see WARNINGS, Anaphylactic Reactions, and PRECAUTIONS, Preexisting Asthma).

Diclofenac sodium extended-release tablets, USP are contraindicated for the treatment of perioperative pain in the setting of coronary artery bypass graft (CABG) surgery (see WARNINGS).

WARNINGS

Cardiovascular Effects

Cardiovascular Thrombotic Events

Clinical trials of several COX-2 selective and nonselective NSAIDs of up to three years duration have shown an increased risk of serious cardiovascular (CV) thrombotic events, myocardial infarction, and stroke, which can be fatal. All NSAIDs, both COX-2 selective and nonselective, may have a similar risk. Patients with known CV disease or risk factors for CV disease may be at greater risk. To minimize the potential risk for an adverse CV event in patients treated with an NSAID, the lowest effective dose should be used for the shortest duration possible. Physicians and patients should remain alert for the development of such events, even in the absence of previous CV symptoms. Patients should be informed about the signs and/or symptoms of serious CV events and the steps to take if they occur.

There is no consistent evidence that concurrent use of aspirin mitigates the increased risk of serious CV thrombotic events associated with NSAID use. The concurrent use of aspirin and an NSAID does increase the risk of serious GI events (see WARNINGS, GI Effects).

Two large, controlled, clinical trials of a COX-2 selective NSAID for the treatment of pain in the first 10-14 days following CABG surgery found an increased incidence of myocardial infarction and stroke (see CONTRAINDICATIONS).

Hypertension

NSAIDs can lead to onset of new hypertension or worsening of preexisting hypertension, either of which may contribute to the increased incidence of CV events. Patients taking thiazides or loop diuretics may have impaired response to these therapies when taking NSAIDs. NSAIDs, including diclofenac sodium extended-release tablets, USP, should be used with caution in patients with hypertension. Blood pressure (BP) should be monitored closely during the initiation of NSAID treatment and throughout the course of therapy.

Congestive Heart Failure and Edema

Fluid retention and edema have been observed in some patients taking NSAIDs. Diclofenac sodium extended-release tablets, USP should be used with caution in patients with fluid retention or heart failure.

Gastrointestinal (GI) Effects: Risk of GI Ulceration, Bleeding, and Perforation

NSAIDs, including diclofenac sodium extended-release tablets, USP, can cause serious gastrointestinal (GI) adverse events including inflammation, bleeding, ulceration, and perforation of the stomach, small intestine, or large intestine, which can be fatal. These serious adverse events can occur at any time, with or without warning symptoms, in patients treated with NSAIDs. Only one in five patients, who develop a serious upper GI adverse event on NSAID therapy, is symptomatic. Upper GI ulcers, gross bleeding, or perforation caused by NSAIDs occur in approximately 1% of patients treated for 3-6 months, and in about 2%-4% of patients treated for one year. These trends continue with longer duration of use, increasing the likelihood of developing a serious GI event at some time during the course of therapy. However, even short-term therapy is not without risk.

NSAIDs should be prescribed with extreme caution in those with a prior history of ulcer disease or gastrointestinal bleeding. Patients with a prior history of peptic ulcer disease and/or gastrointestinal bleeding who use NSAIDs have a greater than 10-fold increased risk for developing a GI bleed compared to patients with neither of these risk factors. Other factors that increase the risk for GI bleeding in patients treated with NSAIDs include concomitant use of oral corticosteroids or anticoagulants, longer duration of NSAID therapy, smoking, use of alcohol, older age, and poor general health status. Most spontaneous reports of fatal GI events are in elderly or debilitated patients and therefore special care should be taken in treating this population.

To minimize the potential risk for an adverse GI event in patients treated with an NSAID, the lowest effective dose should be used for the shortest possible duration.Patients and physicians should remain alert for signs and symptoms of GI ulceration and bleeding during NSAID therapy and promptly initiate additional evaluation and treatment if a serious GI adverse event is suspected. This should include discontinuation of the NSAID until a serious GI adverse event is ruled out. For high risk patients, alternate therapies that do not involve NSAIDs should be considered.

Renal Effects

Caution should be used when initiating treatment with diclofenac sodium extended-release tablets, USP in patients with considerable dehydration.

Long-term administration of NSAIDs has resulted in renal papillary necrosis and other renal injury. Renal toxicity has also been seen in patients in whom renal prostaglandins have a compensatory role in the maintenance of renal perfusion. In these patients, administration of a nonsteroidal anti-inflammatory drug may cause a dose-dependent reduction in prostaglandin formation and, secondarily, in renal blood flow, which may precipitate overt renal decompensation. Patients at greatest risk of this reaction are those with impaired renal function, heart failure, liver dysfunction, those taking diuretics and ACE inhibitors, and the elderly. Discontinuation of non-steroidal anti-inflammatory drug (NSAID) therapy is usually followed by recovery to the pretreatment state.

Advanced Renal Disease

No information is available from controlled clinical studies regarding the use of diclofenac sodium extended-release tablets, USP in patients with advanced renal disease. Therefore, treatment with diclofenac sodium extended-release tablets, USP is not recommended in these patients with advanced renal disease. If diclofenac sodium extended-release tablets, USP therapy must be initiated, close monitoring of the patient's renal function is advisable.

Hepatic Effects

Elevations of one or more liver tests may occur during therapy with diclofenac sodium extended-release. These laboratory abnormalities may progress, may remain unchanged, or may be transient with continued therapy. Borderline elevations (i.e., less than 3 times the ULN [ULN = the upper limit of the normal range]) or greater elevations of transaminases occurred in about 15% of diclofenac-treated patients. Of the markers of hepatic function, ALT (SGPT) is recommended for the monitoring of liver injury.

In clinical trials, meaningful elevations (i.e., more than 3 times the ULN) of AST (GOT) (ALT was not measured in all studies) occurred in about 2% of approximately 5,700 patients at some time during diclofenac treatment. In a large, open-label, controlled trial of 3,700 patients treated for 2-6 months, patients were monitored first at 8 weeks and 1,200 patients were monitored again at 24 weeks. Meaningful elevations of ALT and/or AST occurred in about 4% of patients and included marked elevations (i.e., more than 8 times the ULN) in about 1% of the 3,700 patients. In that open-label study, a higher incidence of borderline (less than 3 times the ULN), moderate (3-8 times the ULN), and marked (>8 times the ULN) elevations of ALT or AST was observed in patients receiving diclofenac when compared to other NSAIDs. Elevations in transaminases were seen more frequently in patients with osteoarthritis than in those with rheumatoid arthritis.

Almost all meaningful elevations in transaminases were detected before patients became symptomatic. Abnormal tests occurred during the first 2 months of therapy with diclofenac in 42 of the 51 patients in all trials who developed marked transaminase elevations.

In postmarketing reports, cases of drug-induced hepatotoxicity have been reported in the first month, and in some cases, the first 2 months of therapy, but can occur at any time during treatment with diclofenac. Postmarketing surveillance has reported cases of severe hepatic reactions, including liver necrosis, jaundice, fulminant hepatitis with and without jaundice, and liver failure. Some of these reported cases resulted in fatalities or liver transplantation.

Physicians should measure transaminases periodically in patients receiving long-term therapy with diclofenac, because severe hepatotoxicity may develop without a prodrome of distinguishing symptoms. The optimum times for making the first and subsequent transaminase measurements are not known. Based on clinical trial data and postmarketing experiences, transaminases should be monitored within 4 to 8 weeks after initiating treatment with diclofenac. However, severe hepatic reactions can occur at any time during treatment with diclofenac.

If abnormal liver tests persist or worsen, if clinical signs and/or symptoms consistent with liver disease develop, or if systemic manifestations occur (e.g., eosinophilia, rash, abdominal pain, diarrhea, dark urine, etc.), diclofenac sodium extended-release tablets, USP should be discontinued immediately.

To minimize the possibility that hepatic injury will become severe between transaminase measurements, physicians should inform patients of the warning signs and symptoms of hepatotoxicity (e.g., nausea, fatigue, lethargy, diarrhea, pruritus, jaundice, right upper quadrant tenderness, and "flu-like" symptoms), and the appropriate action patients should take if these signs and symptoms appear.

To minimize the potential risk for an adverse liver related event in patients treated with diclofenac sodium extended-release tablets, USP, the lowest effective dose should be used for the shortest duration possible. Caution should be exercised in prescribing diclofenac sodium with concomitant drugs that are known to be potentially hepatotoxic (e.g., antibiotics, anti-epileptics).

Anaphylactic Reactions

As with other NSAIDs, anaphylactic reactions may occur both in patients with the aspirin triad and in patients without known sensitivity to NSAIDs or known prior exposure to diclofenac sodium extended-release tablets, USP. Diclofenac sodium extended-release tablets, USP should not be given to patients with the aspirin triad. This symptom complex typically occurs in asthmatic patients who experience rhinitis with or without nasal polyps, or who exhibit severe, potentially fatal bronchospasm after taking aspirin or other NSAIDs. (See CONTRAINDICATIONS and PRECAUTIONS, Preexisting Asthma.) Anaphylaxis-type reactions have been reported with NSAID products, including with diclofenac products, such as diclofenac sodium extended-release tablets, USP. Emergency help should be sought in cases where an anaphylactic reaction occurs.

Skin Reactions

NSAIDs, including diclofenac sodium extended-release tablets, USP, can cause serious skin adverse events such as exfoliative dermatitis, Stevens-Johnson Syndrome (SJS), and toxic epidermal necrolysis (TEN), which can be fatal. These serious events may occur without warning. Patients should be informed about the signs and symptoms of serious skin manifestations and use of the drug should be discontinued at the first appearance of skin rash or any other sign of hypersensitivity.

Pregnancy

In late pregnancy, as with other NSAIDs, diclofenac sodium extended-release tablets, USP should be avoided because it may cause premature closure of the ductus arteriosus.

PRECAUTIONS

General

Diclofenac sodium extended-release tablets, USP cannot be expected to substitute for corticosteroids or to treat corticosteroid insufficiency. Abrupt discontinuation of corticosteroids may lead to disease exacerbation. Patients on prolonged corticosteroid therapy should have their therapy tapered slowly if a decision is made to discontinue corticosteroids.

The pharmacological activity of diclofenac sodium extended-release tablets, USP in reducing fever and inflammation may diminish the utility of these diagnostic signs in detecting complications of presumed noninfectious, painful conditions.

Hematological Effects

Anemia is sometimes seen in patients receiving NSAIDs, including diclofenac sodium extended-release tablets, USP. This may be due to fluid retention, occult or gross GI blood loss, or an incompletely described effect upon erythropoiesis. Patients on long-term treatment with NSAIDs, including diclofenac sodium, should have their hemoglobin or hematocrit checked if they exhibit any signs or symptoms of anemia.

NSAIDs inhibit platelet aggregation and have been shown to prolong bleeding time in some patients. Unlike aspirin, their effect on platelet function is quantitatively less, of shorter duration, and reversible. Patients receiving diclofenac sodium extended-release tablets, USP who may be adversely affected by alterations in platelet function, such as those with coagulation disorders or patients receiving anticoagulants, should be carefully monitored.

Preexisting Asthma

Patients with asthma may have aspirin-sensitive asthma. The use of aspirin in patients with aspirin-sensitive asthma has been associated with severe bronchospasm which can be fatal. Since cross-reactivity, including bronchospasm, between aspirin and other nonsteroidal anti-inflammatory drugs has been reported in such aspirin-sensitive patients, diclofenac sodium extended-release tablets, USP should not be administered to patients with this form of aspirin sensitivity and should be used with caution in all patients with preexisting asthma.

Information for Patients

Patients should be informed of the following information before initiating therapy with an NSAID and periodically during the course of ongoing therapy. Patients should also be encouraged to read the NSAID Medication Guide that accompanies each prescription dispensed.

1. Diclofenac sodium extended-release tablets, USP, like other NSAIDs, may cause serious CV side effects, such as MI or stroke, which may result in hospitalization and even death. Although serious CV events can occur without warning symptoms, patients should be alert for the signs and symptoms of chest pain, shortness of breath, weakness, slurring of speech, and should ask for medical advice when observing any indicative sign or symptoms. Patients should be apprised of the importance of this follow-up (see WARNINGS, Cardiovascular Effects).
2. Diclofenac sodium extended-release tablets, USP, like other NSAIDs, can cause GI discomfort and, rarely, more serious GI side effects, such as ulcers and bleeding, which may result in hospitalization and even death. Although serious GI tract ulcerations and bleeding can occur without warning symptoms, patients should be alert for the signs and symptoms of ulcerations and bleeding, and should ask for medical advice when observing any indicative sign or symptoms including epigastric pain, dyspepsia, melena, and hematemesis. Patients should be apprised of the importance of this follow-up (see WARNINGS, Gastrointestinal Effects: Risk of Ulceration, Bleeding, and Perforation).
3. Diclofenac sodium extended-release tablets, USP, like other NSAIDs, can cause serious skin side effects such as exfoliative dermatitis, SJS, and TEN, which may result in hospitalizations and even death. Although serious skin reactions may occur without warning, patients should be alert for the signs and symptoms of skin rash and blisters, fever, or other signs of hypersensitivity such as itching, and should ask for medical advice when observing any indicative signs or symptoms. Patients should be advised to stop the drug immediately if they develop any type of rash and contact their physicians as soon as possible.
4. Patients should promptly report signs or symptoms of unexplained weight gain or edema to their physicians.
5. Patients should be informed of the warning signs and symptoms of hepatotoxicity (e.g., nausea, fatigue, lethargy, pruritus, jaundice, right upper quadrant tenderness, and “flu-like” symptoms). If these occur, patients should be instructed to stop therapy and seek immediate medical therapy (see WARNINGS, Hepatic Effects).
6. Patients should be informed of the signs of an anaphylactic reaction (e.g., difficulty breathing, swelling of the face or throat). If these occur, patients should be instructed to seek immediate emergency help (see WARNINGS, Anaphylactic Reactions).
7. In late pregnancy, as with other NSAIDs, diclofenac sodium extended-release tablets, USP should be avoided because it will cause premature closure of the ductus arteriosus.

Laboratory Tests

Because serious GI tract ulcerations and bleeding can occur without warning symptoms, physicians should monitor for signs or symptoms of GI bleeding. In patients on long-term treatment with NSAIDs, including diclofenac sodium extended-release tablets, USP, the CBC and a chemistry profile (including transaminase levels) should be checked periodically. If clinical signs and symptoms consistent with liver or renal disease develop, systemic manifestations occur (e.g., eosinophilia, rash, etc.) or if abnormal liver tests persist or worsen, diclofenac sodium extended-release tablets, USP should be discontinued.

Drug Interactions

Aspirin: When diclofenac sodium extended-release tablets, USP are administered with aspirin, its protein binding is reduced. The clinical significance of this interaction is not known; however, as with other NSAIDs, concomitant administration of diclofenac and aspirin is not generally recommended because of the potential of increased adverse effects.

Methotrexate: NSAIDs have been reported to competitively inhibit methotrexate accumulation in rabbit kidney slices. This may indicate that they could enhance the toxicity of methotrexate. Caution should be used when NSAIDs are administered concomitantly with methotrexate.

Cyclosporine: Diclofenac sodium extended-release tablets, USP, like other NSAIDs, may affect renal prostaglandins and increase the toxicity of certain drugs. Therefore, concomitant therapy with diclofenac sodium extended-release tablets, USP may increase cyclosporine’s nephrotoxicity. Caution should be used when diclofenac sodium extended-release tablets, USP are administered concomitantly with cyclosporine.

ACE Inhibitors: Reports suggest that NSAIDs may diminish the antihypertensive effect of ACE inhibitors. This interaction should be given consideration in patients taking NSAIDs concomitantly with ACE inhibitors.

Furosemide: Clinical studies, as well as postmarketing observations, have shown that diclofenac sodium extended-release tablets, USP can reduce the natriuretic effect of furosemide and thiazides in some patients. This response has been attributed to inhibition of renal prostaglandin synthesis. During concomitant therapy with NSAIDs, the patient should be observed closely for signs of renal failure (see WARNINGS, Renal Effects), as well as to assure diuretic efficacy.

Lithium: NSAIDs have produced an elevation of plasma lithium levels and a reduction in renal lithium clearance. The mean minimum lithium concentration increased 15% and the renal clearance was decreased by approximately 20%. These effects have been attributed to inhibition of renal prostaglandin synthesis by the NSAID. Thus, when NSAIDs and lithium are administered concurrently, subjects should be observed carefully for signs of lithium toxicity.

Warfarin: The effects of warfarin and NSAIDs on GI bleeding are synergistic, such that users of both drugs together have a risk of serious GI bleeding higher than users of either drug alone.

CYP2C9 Inhibitors or Inducers: Diclofenac is metabolized by cytochrome P450 enzymes, predominantly by CYP2C9. Co-administration of diclofenac with CYP2C9 inhibitors (e.g. voriconazole) may enhance the exposure and toxicity of diclofenac whereas co-administration with CYP2C9 inducers (e.g. rifampin) may lead to compromised efficacy of diclofenac. Use caution when dosing diclofenac with CYP2C9 inhibitors or inducers, a dosage adjustment may be warranted (see CLINICAL PHARMACOLOGY, Pharmacokinetics, Drug Interactions).

Pregnancy

Teratogenic Effects: Pregnancy Category C

Reproductive studies conducted in rats and rabbits have not demonstrated evidence of developmental abnormalities. However, animal reproduction studies are not always predictive of human response. There are no adequate and well-controlled studies in pregnant women.

Nonteratogenic Effects

Because of the known effects of nonsteroidal anti-inflammatory drugs on the fetal cardiovascular system (closure of ductus arteriosus), use during pregnancy (particularly late pregnancy) should be avoided.

Labor and Delivery

In rat studies with NSAIDs, as with other drugs known to inhibit prostaglandin synthesis, an increased incidence of dystocia, delayed parturition, and decreased pup survival occurred. The effects of diclofenac sodium extended-release tablets, USP on labor and delivery in pregnant women are unknown.

Nursing Mothers

It is not known whether this drug is excreted in human milk. Because many drugs are excreted in human milk and because of the potential for serious adverse reactions in nursing infants from diclofenac sodium extended-release tablets, USP, a decision should be made whether to discontinue nursing or to discontinue the drug, taking into account the importance of the drug to the mother.

Pediatric Use

Safety and effectiveness in pediatric patients have not been established.

Geriatric Use

As with any NSAIDs, caution should be exercised in treating the elderly (65 years and older).

ADVERSE REACTIONS

In patients taking diclofenac sodium extended-release tablets, USP or other NSAIDs, the most frequently reported adverse experiences occurring in approximately 1%-10% of patients are:

Gastrointestinal experiences including: abdominal pain, constipation, diarrhea, dyspepsia, flatulence, gross bleeding/perforation, heartburn, nausea, GI ulcers (gastric/duodenal) and vomiting.

Abnormal renal function, anemia, dizziness, edema, elevated liver enzymes, headaches, increased bleeding time, pruritus, rashes and tinnitus.

Additional adverse experiences reported occasionally include:

Body as a Whole: fever, infection, sepsis

Cardiovascular System: congestive heart failure, hypertension, tachycardia, syncope

Digestive System: dry mouth, esophagitis, gastric/peptic ulcers, gastritis, gastrointestinal bleeding, glossitis, hematemesis, hepatitis, jaundice

Hemic and Lymphatic System: ecchymosis, eosinophilia, leukopenia, melena, purpura, rectal bleeding, stomatitis, thrombocytopenia

Metabolic and Nutritional: weight changes

Nervous System: anxiety, asthenia, confusion, depression, dream abnormalities, drowsiness, insomnia, malaise, nervousness, paresthesia, somnolence, tremors, vertigo

Respiratory System: asthma, dyspnea

Skin and Appendages: alopecia, photosensitivity, sweating increased

Special Senses: blurred vision

Urogenital System: cystitis, dysuria, hematuria, interstitial nephritis, oliguria/polyuria, proteinuria, renal failure.

Other adverse reactions, which occur rarely are:

Body as a Whole: anaphylactic reactions, appetite changes, death

Cardiovascular System: arrhythmia, hypotension, myocardial infarction, palpitations, vasculitis

Digestive System: colitis, eructation, fulminant hepatitis with and without jaundice, liver failure, liver necrosis, pancreatitis

Hemic and Lymphatic System: agranulocytosis, hemolytic anemia, aplastic anemia, lymphadenopathy, pancytopenia

Metabolic and Nutritional: hyperglycemia

Nervous System: convulsions, coma, hallucinations, meningitis

Respiratory System: respiratory depression, pneumonia

Skin and Appendages: angioedema, toxic epidermal necrolysis, erythema multiforme, exfoliative dermatitis, Stevens-Johnson syndrome, urticaria

Special Senses: conjunctivitis, hearing impairment.

OVERDOSAGE

Symptoms following acute NSAID overdoses are usually limited to lethargy, drowsiness, nausea, vomiting, and epigastric pain, which are generally reversible with supportive care. Gastrointestinal bleeding can occur. Hypertension, acute renal failure, respiratory depression and coma may occur, but are rare. Anaphylactoid reactions have been reported with therapeutic ingestion of NSAIDs, and may occur following an overdose.

Patients should be managed by symptomatic and supportive care following a NSAID overdose. There are no specific antidotes. Emesis and/or activated charcoal (60 to 100 g in adults, 1 to 2 g/kg in children) and/or osmotic cathartic may be indicated in patients seen within 4 hours of ingestion with symptoms or following a large overdose (5 to 10 times the usual dose). Forced diuresis, alkalinization of urine, hemodialysis, or hemoperfusion may not be useful due to high protein binding.

DOSAGE AND ADMINISTRATION

Carefully consider the potential benefits and risks of diclofenac sodium extended-release tablets, USP and other treatment options before deciding to use diclofenac sodium extended-release tablets, USP. Use the lowest effective dose for the shortest duration consistent with individual patient treatment goals (see WARNINGS).

After observing the response to initial therapy with diclofenac sodium extended-release tablets, USP, the dose and frequency should be adjusted to suit an individual patient’s needs.

For the relief of osteoarthritis, the recommended dosage is 100 mg q.d.

For the relief of rheumatoid arthritis, the recommended dosage is 100 mg q.d. In the rare patient where diclofenac sodium extended-release tablets, USP 100 mg/day is unsatisfactory, the dose may be increased to 100 mg b.i.d. if the benefits outweigh the clinical risks of increased side effects.

Different formulations of diclofenac (diclofenac sodium enteric-coated tablets; diclofenac sodium extended-release tablets, USP; diclofenac potassium immediate-release tablets) are not necessarily bioequivalent even if the milligram strength is the same.

HOW SUPPLIED

Diclofenac Sodium Extended-Release Tablets, USP

100 mg - round, light pink, biconvex film-coated tablet with beveled edges, with “GG” and “904” printed in black ink on one side and the other side is blank.

Bottles of 100 NDC 0781-1381-01

Do not store above 30ºC (86ºF). Protect from moisture.

Dispense in tight container (USP).

MEDICATION GUIDE

MEDICATION GUIDE FOR NON-STEROIDAL ANTI-INFLAMMATORY DRUGS (NSAIDs)

(See the end of this Medication Guide for a list of prescription NSAID medicines.)

What is the most important information I should know about medicines called Non-Steroidal Anti-Inflammatory Drugs (NSAIDs)?

NSAID medicines may increase the chance of a heart attack or stroke that can lead to death.

This chance increases:

- with longer use of NSAID medicines
- in people who have heart disease

NSAID medicines should never be used right before or after a heart surgery called a "coronary artery bypass graft (CABG)."

NSAID medicines can cause ulcers and bleeding in the stomach and intestines at any time during treatment. Ulcers and bleeding:

- can happen without warning symptoms
- may cause death

The chance of a person getting an ulcer or bleeding increases with:

- taking medicines called "corticosteroids" and "anticoagulants"
- longer use
- smoking
- drinking alcohol
- older age
- having poor health

NSAID medicines should only be used:

- exactly as prescribed
- at the lowest dose possible for your treatment
- for the shortest time needed

What are Non-Steroidal Anti-Inflammatory Drugs (NSAIDs)?

NSAID medicines are used to treat pain and redness, swelling, and heat (inflammation) from medical conditions such as:

- different types of arthritis
- menstrual cramps and other types of short-term pain

Who should not take a Non-Steroidal Anti-Inflammatory Drug (NSAID)?

Do not take an NSAID medicine:

- if you had an asthma attack, hives, or other allergic reaction with aspirin or any other NSAID medicine
- for pain right before or after heart bypass surgery

Tell your healthcare provider:

- about all your medical conditions.
- about all of the medicines you take. NSAIDs and some other medicines can interact with each other and cause serious side effects. Keep a list of your medicines to show to your healthcare provider and pharmacist.
- if you are pregnant. NSAID medicines should not be used by pregnant women late in their pregnancy.
- if you are breastfeeding. Talk to your doctor.

What are the possible side effects of Non-Steroidal Anti-Inflammatory Drugs (NSAIDs)?

Serious side effects include:

- heart attack
- stroke
- high blood pressure
- heart failure from body swelling (fluid retention)
- kidney problems including kidney failure
- bleeding and ulcers in the stomach and intestine
- low red blood cells (anemia)
- life-threatening skin reactions
- life-threatening allergic reactions
- liver problems including liver failure
- asthma attacks in people who have asthma

Other side effects include:

- stomach pain
- constipation
- diarrhea
- gas
- heartburn
- nausea
- vomiting
- dizziness

Get emergency help right away if you have any of the following symptoms:

- shortness of breath or trouble breathing
- chest pain
- weakness in one part or side of your body
- slurred speech
- swelling of the face or throat

Stop your NSAID medicine and call your healthcare provider right away if you have any of the following symptoms:

- nausea
- more tired or weaker than usual
- itching
- your skin or eyes look yellow
- stomach pains
- flu-like symptoms
- vomit blood
- there is blood in your bowel movement or it is black and sticky like tar
- unusual weight gain
- skin rash or blisters with fever
- swelling of the arms and legs, hands and feet

These are not all the side effects with NSAID medicines. Talk to your healthcare provider or pharmacist for more information about NSAID medicines. Call your doctor for medical advice about side effects. You may report side effects to FDA at 1-800-FDA-1088.

Other information about Non-Steroidal Anti-Inflammatory Drugs (NSAIDs)

- Aspirin is an NSAID medicine but it does not increase the chance of a heart attack. Aspirin can cause bleeding in the brain, stomach, and intestines. Aspirin can also cause ulcers in the stomach and intestines.
- Some of these NSAID medicines are sold in lower doses without a prescription (over the counter). Talk to your healthcare provider before using over the counter NSAIDs for more than 10 days.

NSAID medicines that need a prescription

Generic Name | Tradename
Celecoxib | Celebrex
Diclofenac | Cataflam, Voltaren, Arthrotec (combined with misoprostol)
Diflunisal | Dolobid
Etodolac | Lodine, Lodine XL
Fenoprofen | Nalfon, Nalfon 200
Flurbiprofen | Ansaid
Ibuprofen | Motrin, Tab-Profen, Vicoprofen* (combined with hydrocodone), Combunox (combined with oxycodone)
Indomethacin | Indocin, Indocin SR, Indo-Lemmon, Indomethagan
Ketoprofen | Oruvail
Ketorolac | Toradol
Mefenamic Acid | Ponstel
Meloxicam | Mobic
Nabumetone | Relafen
Naproxen | Naprosyn, Anaprox, Anaprox DS, EC-Naproxyn, Naprelan, Naprapac (copackaged with lansoprazole)
Oxaprozin | Daypro
Piroxicam | Feldene
Sulindac | Clinoril
Tolmetin | Tolectin, Tolectin DS, Tolectin 600

* Vicoprofen contains the same dose of ibuprofen as over-the-counter (OTC) NSAIDs, and is usually used for less than 10 days to treat pain. The OTC NSAID label warns that long term continuous use may increase the risk of heart attack or stroke.

The brands listed are the trademarks or register marks of their respective owners.

This Medication Guide has been approved by the U.S. Food and Drug Administration.

T2013-16/T2009-39
February 2011/March 2009

Manufactured by
Novartis Pharma Stein AG
Stein, Switzerland for
Sandoz Inc.
Princeton, NJ 08540